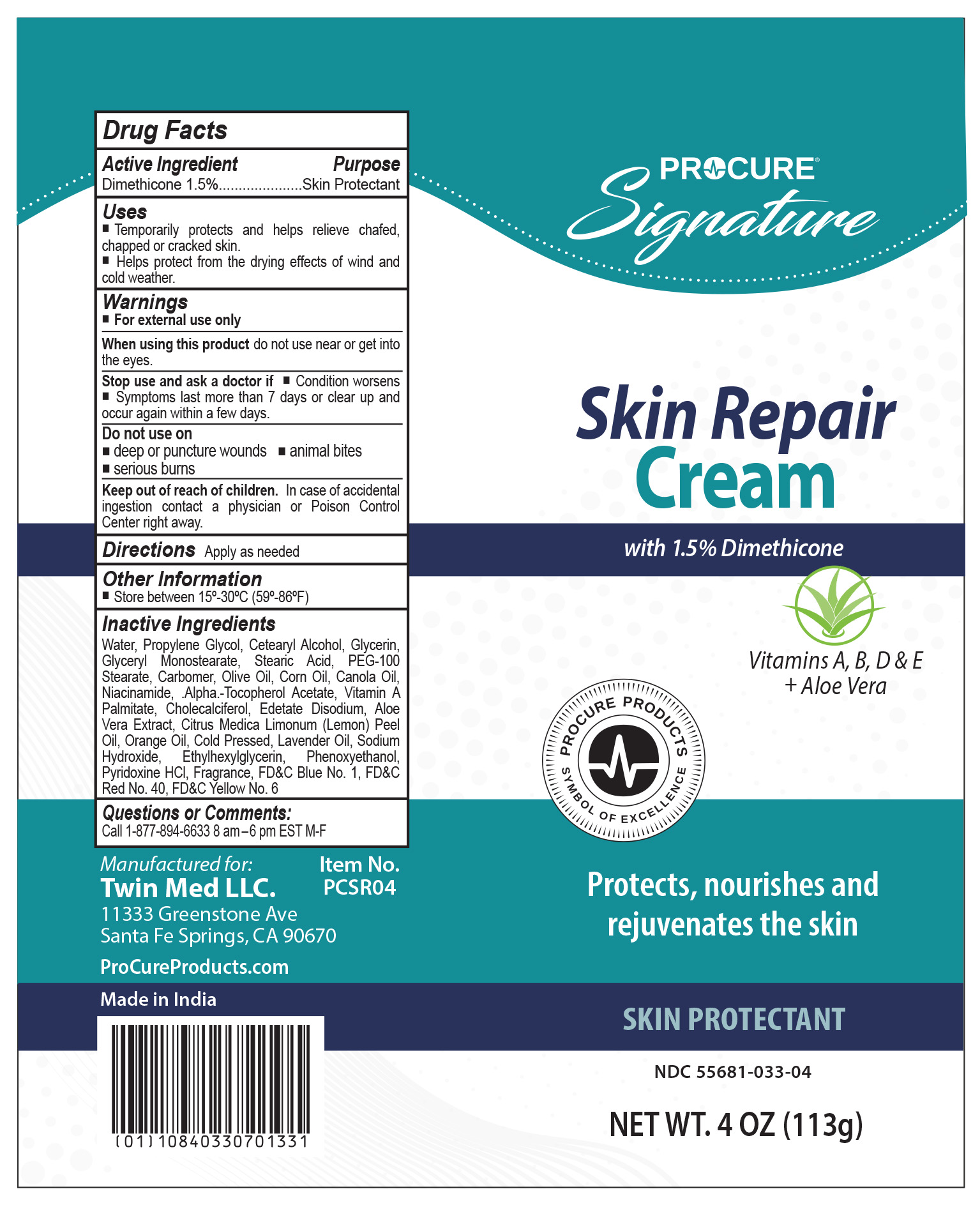 DRUG LABEL: ProCure Skin Repair Cream
NDC: 55681-033 | Form: CREAM
Manufacturer: Twin Med LLC
Category: otc | Type: HUMAN OTC DRUG LABEL
Date: 20250805

ACTIVE INGREDIENTS: DIMETHICONE, UNSPECIFIED 1.5 g/100 g
INACTIVE INGREDIENTS: CARBOMER HOMOPOLYMER, UNSPECIFIED TYPE; CORN OIL; PYRIDOXINE HCL; FD&C BLUE NO. 1; FD&C YELLOW NO. 6; CHOLECALCIFEROL; STEARIC ACID; PEG-100 STEARATE; OLIVE OIL; NIACINAMIDE; LEMON OIL, COLD PRESSED; ORANGE OIL, COLD PRESSED; VITAMIN A PALMITATE; CETEARYL ALCOHOL; GLYCERIN; GLYCERYL MONOSTEARATE; CANOLA OIL; LAVENDER OIL; FD&C RED NO. 40; ETHYLHEXYLGLYCERIN; SODIUM HYDROXIDE; WATER; EDETATE DISODIUM; ALOE VERA LEAF; PHENOXYETHANOL; PROPYLENE GLYCOL; .ALPHA.-TOCOPHEROL ACETATE

Active Ingredient

Dimethicone 1.5%

Purpose

Skin Protectant

Uses

- Temporarily protects and helps relieve chafed, chapped or cracked skin
- Helps protect from the drying effects of wind and cold weather

Warnings

For external use only

When using this product do not use near or get into the eyes.

Stop use and ask a doctor if

- Condition worsens
- Symptoms last more than 7 days or clear up and occur again within a few days

Do not use on deep or puncture wounds, animal bites, serious burns

Keep out of reach of children. In case of accidental ingestion contact a physician or Poison Control Center right away.

Directions

Apply as needed

Inactive Ingredients

Water, Propylene Glycol, Cetearyl Alcohol, Glycerin, Glyceryl Monostearate, Stearic Acid, PEG-100 Stearate, Carbomer, Olive Oil, Corn Oil, Canola Oil, Niacinamide, .Alpha.-Tocopherol Acetate, Vitamin A Palmitate, Cholecalciferol, Edetate Disodium, Aloe Vera Extract, Citrus Medica Limonum (Lemon) Peel Oil, Orange Oil, Cold Pressed, Lavender Oil, Sodium Hydroxide, Ethylhexylglycerin, Phenoxyethanol, Pyridoxine HCl, Fragrance, FD&C Blue No. 1, FD&C Red No. 40, FD&C Yellow No. 6